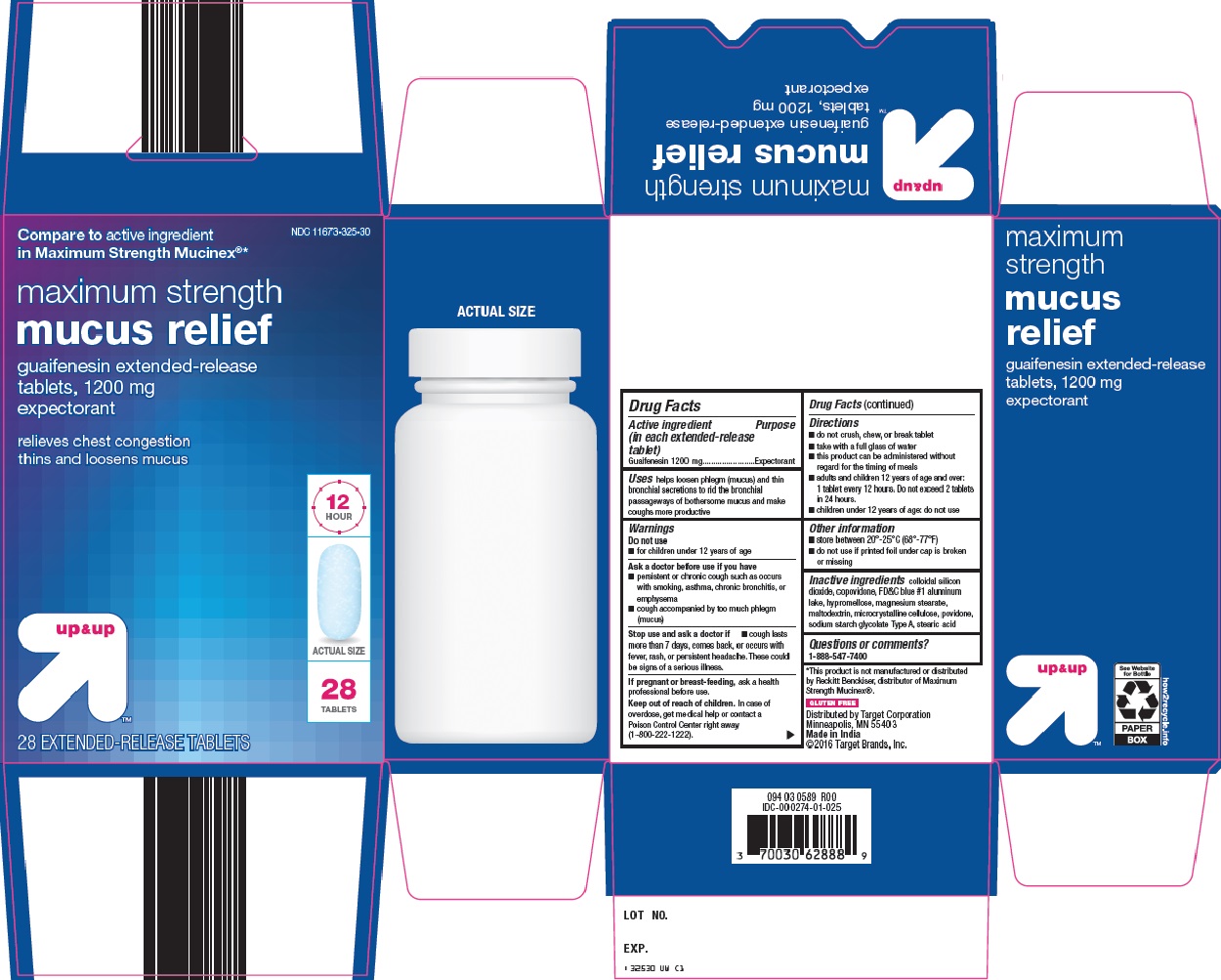 DRUG LABEL: Up and Up mucus relief
NDC: 11673-325 | Form: TABLET, EXTENDED RELEASE
Manufacturer: Target Corporation
Category: otc | Type: HUMAN OTC DRUG LABEL
Date: 20191107

ACTIVE INGREDIENTS: GUAIFENESIN 1200 mg/1 1
INACTIVE INGREDIENTS: SILICON DIOXIDE; COPOVIDONE K25-31; FD&C BLUE NO. 1; MAGNESIUM STEARATE; MALTODEXTRIN; MICROCRYSTALLINE CELLULOSE; STEARIC ACID

Target Corporation Mucus Relief Drug Facts

Active ingredient (in each extended-release tablet)

Guaifenesin 1200 mg

Purpose

Expectorant

Uses

helps loosen phlegm (mucus) and thin bronchial secretions to rid the bronchial passageways of bothersome mucus and make coughs more productive

Warnings

Do not use

- for children under 12 years of age

Ask a doctor before use if you have

- persistent or chronic cough such as occurs with smoking, asthma, chronic bronchitis, or emphysema
- cough accompanied by too much phlegm (mucus)

Stop use and ask a doctor if

- cough lasts more than 7 days, comes back, or occurs with fever, rash, or persistent headache. These could be signs of a serious illness.

If pregnant or breast-feeding,

ask a health professional before use.

Keep out of reach of children.

In case of overdose, get medical help or contact a Poison Control Center right away (1-800-222-1222).

Directions

- do not crush, chew, or break tablet
- take with a full glass of water
- this product can be administered without regard for the timing of meals
- adults and children 12 years of age and over: 1 tablet every 12 hours. Do not exceed 2 tablets in 24 hours.
- children under 12 years of age: do not use

Other information

- store between 20°-25°C (68°-77°F)
- do not use if printed foil under cap is broken or missing

Inactive ingredients

colloidal silicon dioxide, copovidone, FD&C blue #1 aluminum lake, hypromellose, magnesium stearate, maltodextrin, microcrystalline cellulose, povidone, sodium starch glycolate Type A, stearic acid

Questions or comments?

1-888-547-7400

Package/Label Principal Display Panel

Compare to active ingredient in Maximum Strength Mucinex®

maximum strength

mucus relief

guaifenesin extended-release tablets, 1200 mg

expectorant

relieves chest congestion

thins land loosens mucus

12 HOUR

ACTUAL SIZE

28 TABLETS

28 EXTENDED-RELEASE TABLETS